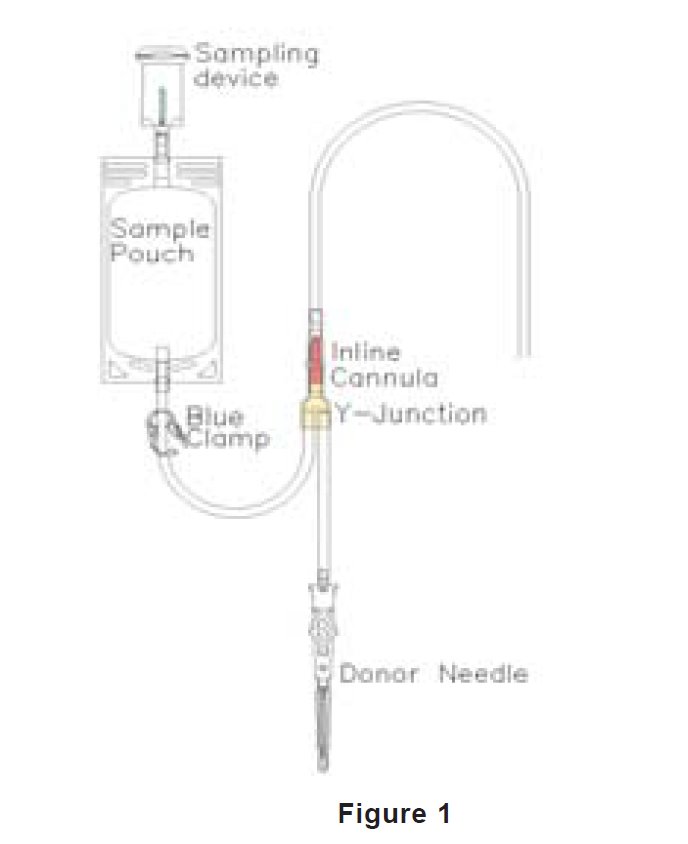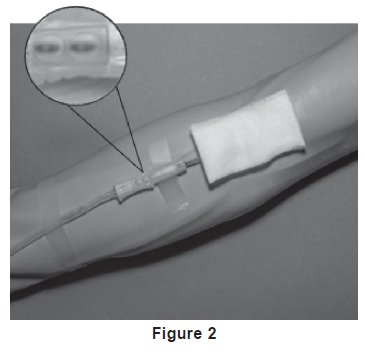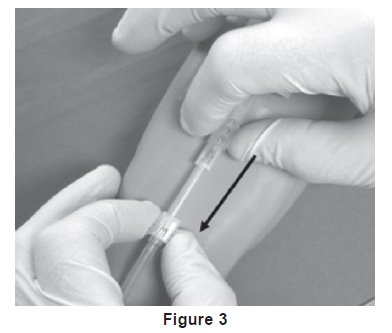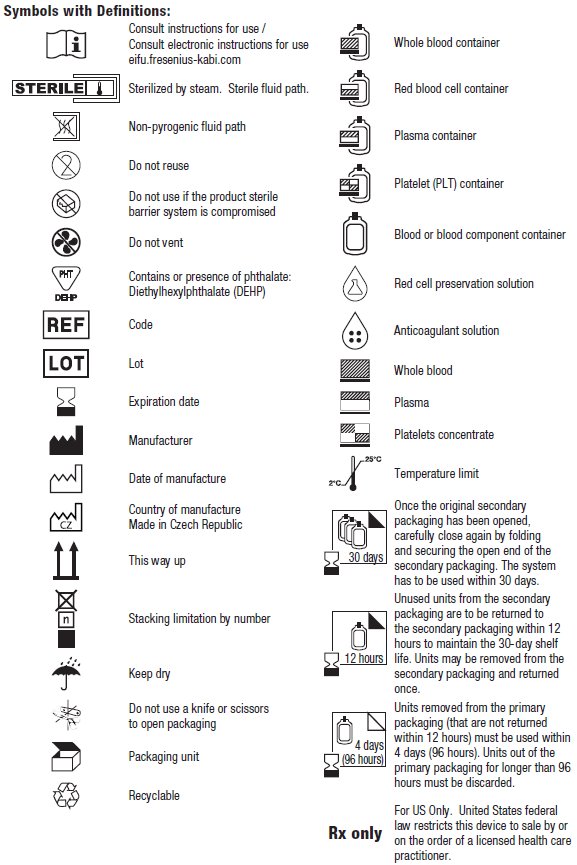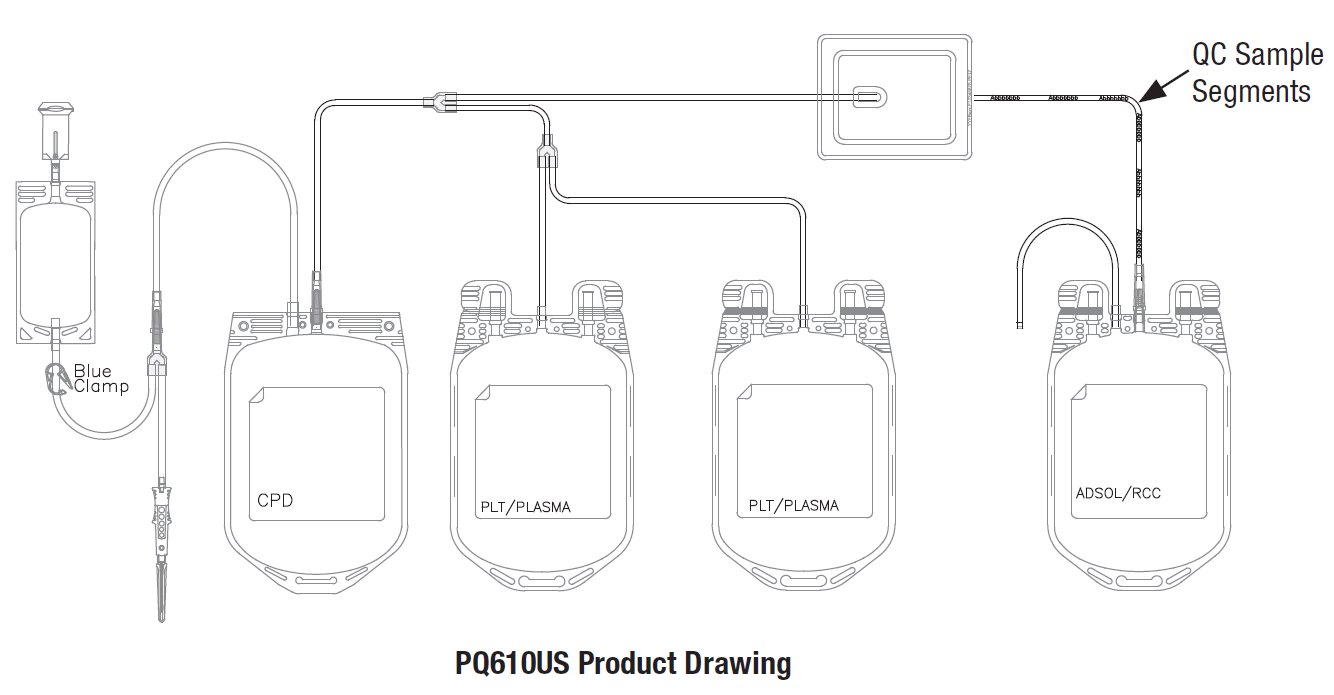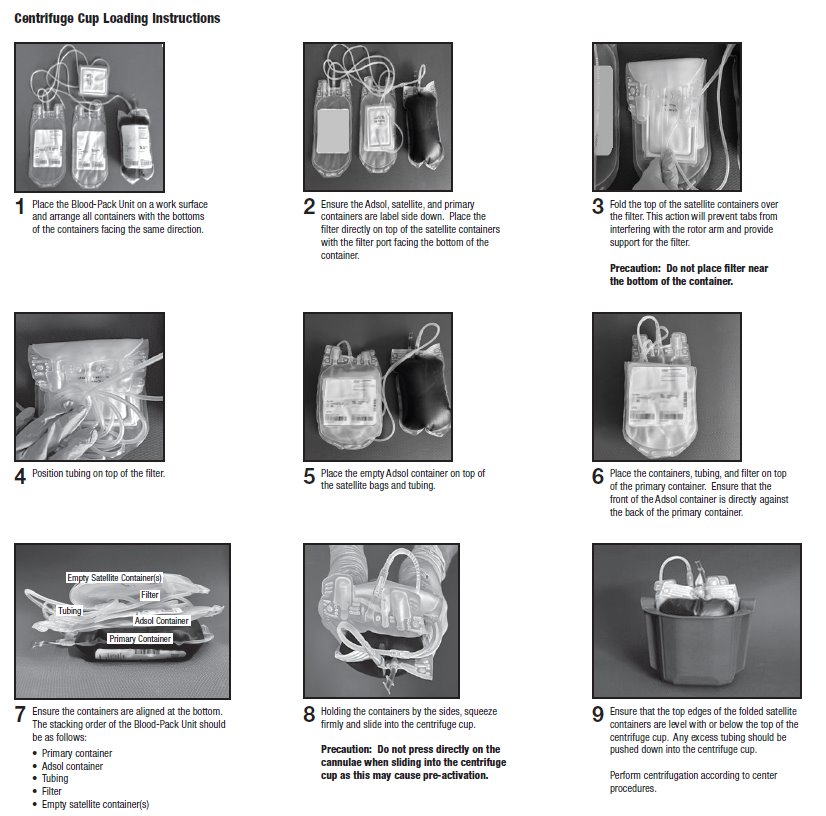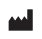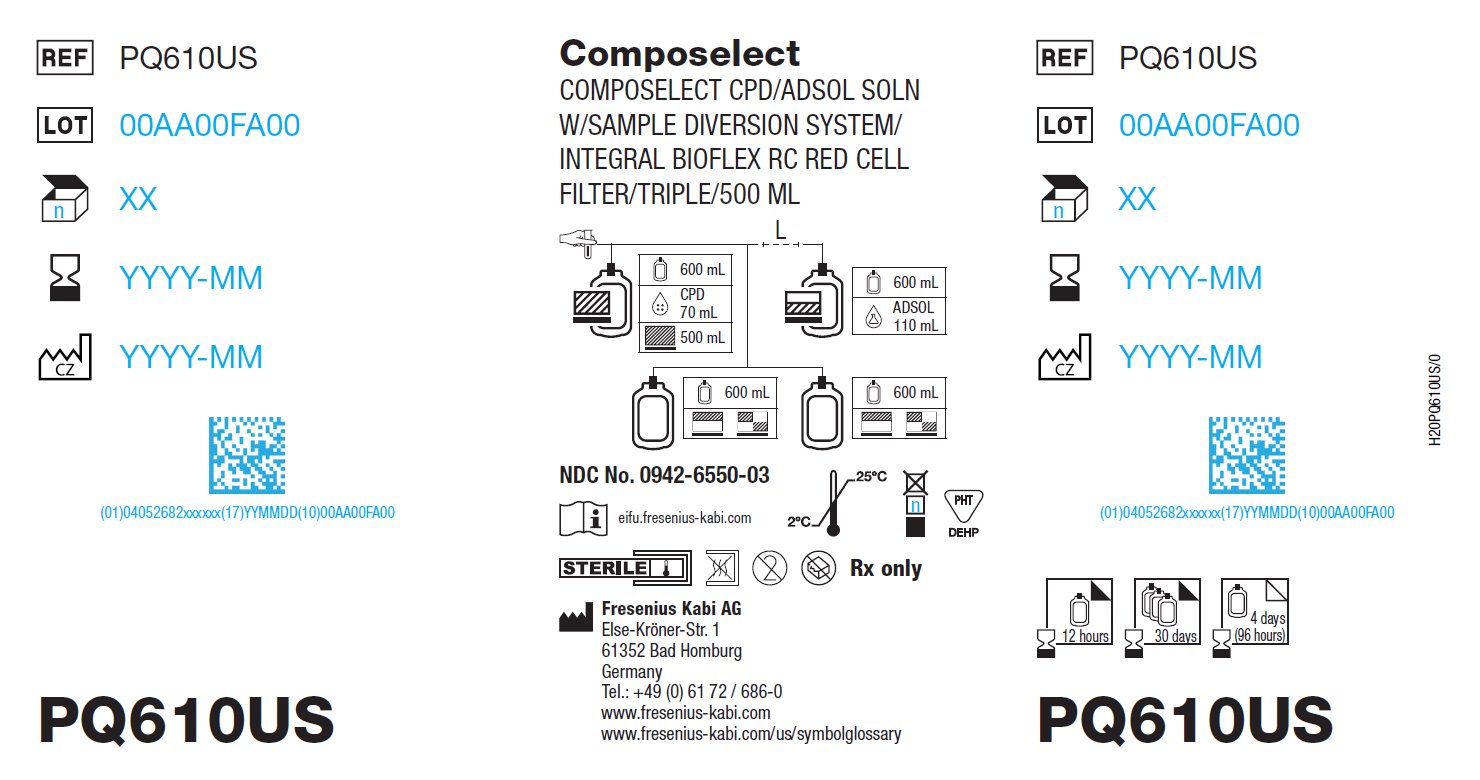 DRUG LABEL: ADSOL RED CELL PRESERVATION
NDC: 0942-6550 | Form: KIT | Route: INTRAVENOUS
Manufacturer: Fenwal, Inc.
Category: prescription | Type: HUMAN PRESCRIPTION DRUG LABEL
Date: 20251105

ACTIVE INGREDIENTS: TRISODIUM CITRATE DIHYDRATE 1.84 g/70 mL; DEXTROSE MONOHYDRATE 1.78 g/70 mL; ANHYDROUS CITRIC ACID 229 mg/70 mL; SODIUM PHOSPHATE, MONOBASIC, DIHYDRATE 176 mg/70 mL; DEXTROSE MONOHYDRATE 2.42 g/110 mL; SODIUM CHLORIDE 990 mg/110 mL; MANNITOL 825 mg/110 mL; ADENINE 30 mg/110 mL
INACTIVE INGREDIENTS: WATER

REF PQ610US NDC No. 0942-6550-01 20x Rx only
Fresenius Kabi
Composelect System with Fenwal HighFlo Needle for Collection of Whole Blood using CPD/Adsol Red Cell Preservation Solution and an Integral Fenwal Bioflex RC Leukocyte Reduction Filter for Filtration of Red Blood Cells.

Contains Sample Diversion System for the collection of unanticoagulated whole blood samples for laboratory testing.

Description

The Composelect System is a triple configuration intended for use in collecting Whole Blood and separation of blood components including Red Blood Cells, Plasma, and Platelets.

The Composelect system has a sterile, non-pyrogenic fluid path and is intended for single use only.

Integral filter unit intended for leukocyte reduction of AS-1 red blood cells:

- At ambient temperature up to 8 hours after blood collection.
- At refrigerated temperature (1°C to 6°C) up to 3 days after blood collection if AS-1 red blood cells are prepared within 3 days after whole blood collection.

The leukocyte reduced red blood cells may then be stored for up to 42 days after collection.

Platelets prepared and stored in the satellite container included in the Composelect system can be

stored for 5 days at 20°C to 24°C.

General Precautions

- Store at controlled room temperature, from 20°C to 25°C (68°F to 77°F). Excursions between 15°C and 30°C (59°C and 86°F) with transient spikes up to 40°C are permitted as long as they do not exceed 24 hours.
Reference: United States Pharmacopeia, General Notices. United States Pharmacopeial Convention, Inc. 12601 Twinbrook Parkway, Rockville, MD.
- Protect from freezing.
- Avoid excessive heat.
- Do not squeeze or fold the filter
- Inadequate clamping of the donation line can cause non-sterile air to enter the collection container once the needle cover has been removed.
- Use the cannula activation tool (cannula cracker) or qualified automated system only to open the X-Breaker in the top seal of the primary (CPD) and Adsol containers. Do not use the tool to open the cannula in the donor lead. This must be opened manually. See Figure 1.
- Once the original secondary packaging has been opened, carefully close again by folding and securing the open end of the secondary packaging. The system has to be used within 30 days.
- Unused units from the secondary packaging are to be returned to the secondary packaging within 12 hours to maintain the 30-day shelf life. Units may be removed from the secondary packaging and returned once.
- Units removed from the primary packaging (that are not returned within 12 hours) must be used within 4 days (96 hours). Units out of the primary packaging for longer than 96 hours must be discarded.

Directions for Use

Pre-collection Inspection

Examine the collection container and storage containers. Do not use the container if you observe any of the following:

- Visible damage, defects or non-conformity to the product representing a risk to the integrity of the system
- Solutions are unusual color, not clear, or contain particulate matter
- Kinks and large dents in the tubing
- Damaged or loose components of the product
- In-line cannula is broken and/or anticoagulant is present in the sample pouch or in the tubing from the in-line cannula to the sample pouch and donor needle (see Figure 1)
- Labels on the containers are absent, damaged, or defaced.

Note: Condensation in the empty tubing of the Composelect System is expected as a result of the sterilization process.

Collection Procedure

Use aseptic technique.

1. Identify Composelect System using appropriate donor identification system.

2. Adjust donor scale to desired collection weight and position the Composelect system on the donor scale as far as possible below donor arm.

Note: When using a Composelect System on a donor scale, ensure that the filter is not placed between the containers as this could cause improper mixing of the blood with anticoagulant.

3. Unwind the tubing and ensure it is torsion-free to prevent the needle from turning while drawing blood. See Figure 1.

4. Clamp donor tubing between Fenwal HighFlo^1 needle and Y-junction with a clamp. (This step may be performed prior to step 1 or 2.)

Notes: Ensure that the sample pouch remains below the donor’s arm.

5. Following facility procedures, disinfect site of venipuncture, then apply pressure to donor’s arm.

6. Remove Fenwal HighFlo^1 needle cover per instructions below:

a) Holding the hub and cover near tamper-evident seal, twist cover and hub in opposite directions to break seal.
b) Remove and discard needle cover, being careful not to drag the cover across the needle point.

7. Following facility procedures, perform venipuncture and appropriately secure donor needle and/or tubing. When good blood flow is established, stabilize the front of the needle guard to arm with tape (see Figure 2).

8. Allow the sample pouch to fill with blood according to center procedure. Monitor blood flow into sample pouch.

Precautions:

- Do not elevate or squeeze the sample pouch as this could cause blood to backflow from the sample pouch into the collection system.
- Once the sample pouch is filled to desired volume, complete steps 9 – 15 within approximately 4 minutes to avoid possible clot formation in the tubing and/or sample pouch.

9. Close the blue clamp on tubing between the Y-junction and the sample pouch.

10. Break the in-line cannula below the Y-junction in the donor tubing to the primary container allowing blood collection to proceed. To completely break the in-line cannula, grasp with both hands. Snap it at a 90° angle in one direction, and then bend it at a 90° angle in the opposite direction. Ensure the inline

cannula is completely broken and that the blood flows freely to the primary container.

Precaution:

- The in-line cannula must be opened by hand. Do not use any manual hand opening tools, such as the Fenwal Cannula Cracker.
- Failure to break the in-line cannula completely may result in restricted blood flow.

Note: Mix blood and anticoagulant in the primary container immediately, at several intervals during collection, and immediately after collection.

11. Following blood center procedures, hermetically seal the tubing between the sampling site and the Y-junction to maintain sterility of the blood collection system prior to removing blood samples.

Warning:

Do not proceed with the remaining steps until the tubing leading to the sample pouch is hermetically sealed between the sampling site and the Y-junction. To maintain the whole blood

collection container as a closed system, the tubing between the sample pouch and Y-junction must be hermetically sealed prior to inserting the access device into the sampling site. Failure to do so may lead to contamination of the whole blood collection.

12. To collect samples, open the cap of the sample access device, then hold the sample pouch in an upright position with the access device pointing downwards.

13. Directly align the vacuum sample tube with the internal needle in the access device. Insert vacuum sample tube into device until the stopper is punctured.

14. Allow vacuum sample tube to fill with blood then remove from the access device.

Note: Don’t squeeze the sample pouch.

15. Repeat steps 13 and 14 until the desired number of vacuum sample tubes have been filled.

16. Collect 500 mL ±10% (450 - 550 mL) volume of blood.

Note: The volume of anticoagulant is sufficient for the blood collection indicated on the Composelect System ± 10%.

Precaution: Once the desired blood volume is collected, complete steps 17 to 22 within approximately 4 minutes to avoid possible clot formation in the tubing.

17. Release pressure on donor's arm. Apply clamp to donor tubing between needle and the Y-junction.

18. Hermetically seal donor tubing between the in-line cannula and the primary container.

19. Withdrawal of Needle (see Figure 3).

Precaution: The needle guard must be held stationary while the needle is withdrawn into it.

a) Place folded sterile gauze over puncture site and hold in place with finger tip without exerting pressure.
b) Hold sides of needle guard near the front, between the index finger and thumb. Pull the hub back smoothly until the needle is completely enclosed and securely locked into the needle guard.
c) Confirm the needle is completely enclosed and securely locked into the needle guard.

20. Grip the retracted needle by the needle hub and place the needle into the sample access device, then close the cap to secure the needle.

21. Remove and discard the sampling system and needle guard into an appropriate biohazardous waste container following facility procedures. If donor tubing is also to be discarded, hermetically seal donor tubing directly above the primary container and remove.

22. If the donor tubing is not hermetically sealed directly above the primary container, then strip the blood from the remaining donor tubing into the primary container and mix. If desired, allow tubing to refill.

23. Follow your facility procedure to place the unit into appropriate temporary storage at ambient temperature or with sufficient coolant to lower the temperature continuously toward 1-10 °C until delivered to the component processing facility.

Component Preparation

Notes:

- If a platelet concentrate is to be prepared, it should be separated within 8 hours after blood collection.
- Fresh frozen plasma should be separated from the red blood cells and placed in the freezer at -18°C or colder within 8 hours after blood collection.
- Adsol red cell preservation solution should be added to the red blood cells immediately after the removal of plasma.
- Preparation of AS-1 red blood cells may vary depending on processing option selected:
a) Within 8 hours of blood collection if whole blood is held at ambient temperature.
b) Within 3 days of blood collection if whole blood is stored at 1°C - 6°C.

24. At the appropriate time, prepare the Composelect System for centrifugation.

25. Thoroughly mix the primary container end over end.

26. Load the containers into a centrifuge cup per the instructions on page 4.

Notes:

- This guide is one method for centrifuge cup loading. The specific stacking order and methods may vary depending on the workstation setup, centrifuge equipment, and facility-specific Standard Operating Procedures.
- It is important to pack the filter properly in the centrifugation cup to avoid damage to the filter during centrifugation.
- Do not place the filter in the lower half of the centrifuge cup. See step 3 on page 4 for proper placement of filter.
- Do not press directly on the cannulae while performing any of the cup loading steps as this may cause pre-activation of the cannulae.

27. After loading the Composelect System into the centrifuge cup, perform centrifugation according to facility procedures.

28. Following centrifugation, remove containers from the centrifuge cup, taking care not to disturb the red blood cell / plasma interface.

29. Place primary container in a plasma extractor and apply pressure. Clamp off tubing above the filter to prevent plasma flow into filter during plasma transfer. Clamp off tubing below Y-junction leading to secondary Transfer Pack container not to be filled with plasma. Open the cannula on the top of the primary container to transfer plasma into the empty transfer pack container.

Note: A manual tool or automated breaker may be used to open the cannula on the top of the primary

container.

30. When the desired amount of plasma has been removed, clamp the tubing between the plasma container and the Y-junction closest to the plasma container and release pressure on the primary container.

31. Hermetically seal and remove satellite containers.

Addition of Adsol to Red Cells

32. Position the Adsol red cell preservation solution container ensuring that the primary container remains below the level of the filter during prime.

33. Open the cannula on the Adsol solution container and remove the clamp between the primary container and the filter.

Note: A manual tool or automated breaker may be used to open the cannula on the top of the Adsol solution container.

34. Transfer the Adsol through the filter into the primary container.

35. After prime is complete, clamp the tubing between the filter and primary container.

36. Mix the Adsol red cell preservation solution and red cells thoroughly.

Notes:

- If the Adsol red cell preservation solution is not added to the red cells, ensure appropriate labeling of the red cell container. Also ensure that tubing with unique segment numbers are attached, as the primary container does not include tubing with segment numbers. Manufacture of CPD red cells for transfusion must include proper labeling of the container, as well as attached tubing, with unique segment numbers.
- A CPD red cell without Adsol red cell preservation solution may be stored between 1ºC and 6ºC up to 21 days after collection. The attached Bioflex RC filter should not be used to leukoreduce a CPD red cell product without Adsol red cell preservation solution and should be detached from the primary container.
- CPD Red Blood Cells without Adsol can be leukoreduced using an appropriate “dock-on” filter.

Integral Red Cell Filtration

Precaution: Red blood cell products collected from certain donors may have extended filtration times and the potential for ineffective filtration and leukoreduction.

37. Mix unfiltered AS-1 red blood cells thoroughly. Invert the unfiltered AS-1 red blood cells and hang the filter set such that the filter remains vertical. To achieve maximum flow rate, allow the set to hang to full length. The storage container must remain below the level of the filter during filtration.

38. Filtration must be initiated within 8 hours after collection if Red Blood cells are maintained at ambient temperature and filtration is performed at ambient temperature or within 3 days after collection if Red Blood Cells are stored at 1°C - 6°C and filtration is performed at 1°C - 6°C

39. Inspect all tubing to ensure it hangs freely without kinks.

40. Remove the clamp above the filter to start filtration.

Note: Manual or mechanical pressure should not be used to increase the flow rate through the filter. Tubing below the filter should not be stripped at any time during the filtration process.

Note: If filtration of red cells is initiated at ambient temperature, the filtration process can be completed at either ambient or refrigerated temperature prior to storing the red cells between 1° and 6°C. However, for optimal filtration time, it is recommended to complete the filtration at ambient temperature.

41. When filtration is complete, air can be observed in the inlet side of the filter. Hermetically seal and detach the tubing below the filter.

42. Make segments on the post-filter tubing as indicated on the product diagram, and leave segments attached to the leukoreduced red cell storage container. QC samples may be prepared by stripping the red blood cells in the tubing, thoroughly mixing the red blood cells, then refilling the tubing and sealing the segments. Discard the filter and the empty primary container.

43. Store the AS-1 red blood cells, leukocytes reduced between 1ºC and 6°C.

44. Transfuse the red cells within 42 days of collection.

45. Quality control testing of Red Blood Cells, AS-1 Added, Leukocytes Reduced, including testing for residual white blood cells, should be performed in accordance with regulatory requirements.

Warning: Failure to achieve closed system processing conditions negates the extended storage claim and the red blood cell product must be transfused within 24 hours.

46. Dispose of waste in appropriate biohazard container or according to local regulatory requirements.

Note: Commercially available spacers (such as a Blood Bag Insert or similar) or other methods may be followed to take up space in the cup. When used, the spacer must be placed between the empty satellite

containers and the centrifuge cup.

^1 Van der Meer, P.F., & de Korte, D. “Increase of blood donation speed by optimizing the needle-to-tubing connection: an application of donation software.” Vox Sanguinis 2009, 97: 21-25

Fresenius Kabi AG

Else-Kröner-Str. 1

61352 Bad Homburg

Germany

Tel.: +49 (0) 61 72 / 686-0

www.fresenius-kabi.com

www.fresenius-kabi.com/us/symbolglossary

© 2025 Fresenius Kabi AG. All rights reserved.

All trademarks referred to are property of their respective owners.

33839 [E] 2025/10

PACKAGE LABEL PRINCIPAL DISPLAY PANEL

COMPOSELECT CPD/ADSOL SOLN W/SAMPLE DIVERSION SYSTEM/INTEGRAL BIOFLEX RC RED CELL FILTER/TRIPLE/500 ML